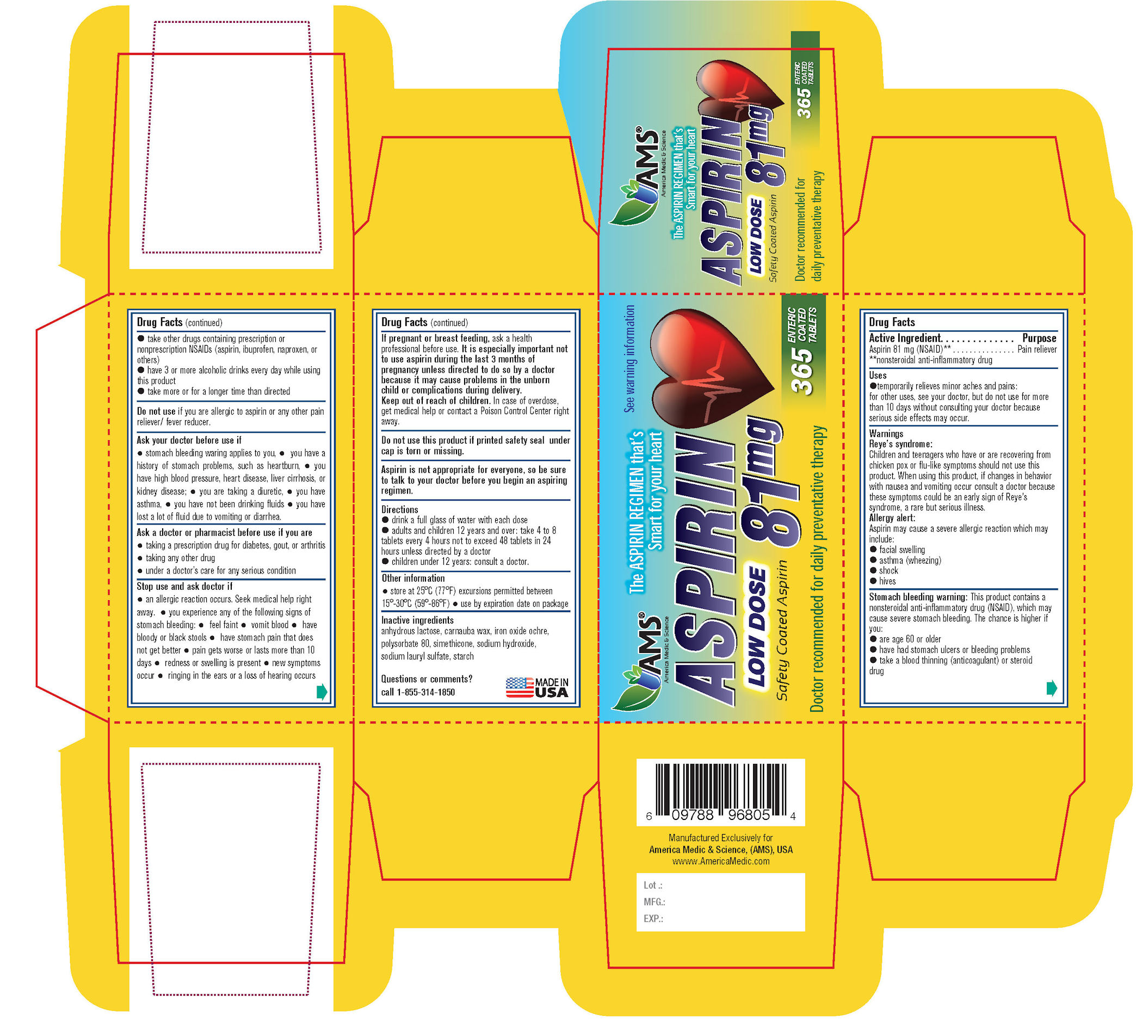 DRUG LABEL: Aspirin
NDC: 49638-481 | Form: TABLET
Manufacturer: America Medic & Science
Category: otc | Type: HUMAN OTC DRUG LABEL
Date: 20170118

ACTIVE INGREDIENTS: ASPIRIN 81 mg/1 1
INACTIVE INGREDIENTS: STARCH, CORN; SODIUM LAURYL SULFATE; ANHYDROUS LACTOSE; POLYSORBATE 80; SODIUM HYDROXIDE; CARNAUBA WAX; BROWN IRON OXIDE; DIMETHICONE

Aspirin 81 mg Low Dose
Safety Coated Aspirin

Drug Facts

Active ingredient (in each tablet)

Aspirin, 81 mg (NSAID)*

*nonsteroidal anti-inflammatory drug

Purpose

Pain reliever

Uses

- temporarily relieves minor aches and pains
- for other uses, see your doctor, but do not use for more than 10 days without consulting your doctor because serious side effects may occur.

Warnings

Reye's syndrome: Children and teenagers who have or are recovering from chicken pox or flu-like symptoms should not use this product. When using this product, if changes in behavior with nausea and vomiting occur, consult a doctor because these symptoms could be an early sign of Reye's syndrome, a rare but serious illness.

Allergy alert: Aspirin may cause a severe allergic reaction which may include

- facial swelling
- asthma (wheezing)
- shock
- hives

Stomach bleeding warning: This product contains a nonsteroidal anti-inflammatory drug (NSAID), which may cause severe stomach bleeding. The chance is higher if you:

- are age 60 or older
- have had stomach ulcers or bleeding problems
- take a blood thinning (anticoagulant) or steriod drug
- take other drugs containing prescription or non-prescription NSAIDs (aspirin, ibuprofen, naproxen, or others)
- have 3 or more alcoholic drinks every day while using this product
- take more or for a longer time than directed

Do not use if you are allergic to aspirin or any other pain reliever/ fever reducer.

Ask a doctor before use if

- stomach bleeding warning applies to you
- you have a history of stomach problems, such as heartburn
- you have high blood pressure, heart disease, liver cirrhosis, or kidney disease
- you are taking a diuretic
- you have asthma
- you have not been drinking fluids
- you have lost a lot of fluid due to vomiting or diarrhea

Ask a doctor or pharmacist before use if you are

- taking a prescription drug for diabetes, gout or arthritis
- taking any other drug
- under a doctor's care for any serious condition

Stop use and ask a doctor if

- an allergic reaction occurs. Seek medical help right away.
- you experience any of the following signs of stomach bleeding:
- feel faint
- vomit blood
- have bloody or black stools
- have stomach pain that does not get better
- pain gets worse or lasts more than 10 days
- redness or swelling is present
- fever gets worse or lasts more than 3 days
- new symptoms occur
- ringing in the ear or loss of hearing occurs

PREGNANCY OR BREAST FEEDING

If pregnant or breast-feeding, ask a health professional before use. It is especially important not to use aspirin during the last 3 months of pregnancy unless definitely directed to do so by a doctor because it may cause problems in the unborn child or complictions during delivery.

Keep out of reach of children. In case of overdose, get medical help or contact a Poison Control Center right away.

Do not use this product if printed safety seal under cap is torn or missing.

Aspirin is not appropriate for everyone, so be sure to talk to your doctor before you begin an aspiring regimen.

Directions

- drink a full glass of water with each dose
- adults and children 12 years and over: take 4 to 8 tablets every 4 hours not to exceed 48 tablets in 24 hours unless directed by a doctor
- children under 12 years: consult a doctor.

Other information

- store at 25°C (77°F) excursions permitted between 15°-30°C (59°-86°F)
- use by expiration date on package

INACTIVE INGREDIENT

anhydrous lactose, carnauba wax, iron oxide ochre, polysorbate 80, simethicone, sodium hydroxide, sodium lauryl sulfate, starch

Questions or comments?

call 1-855-314-1850

PACKAGE LABEL

NDC 49638-481-36